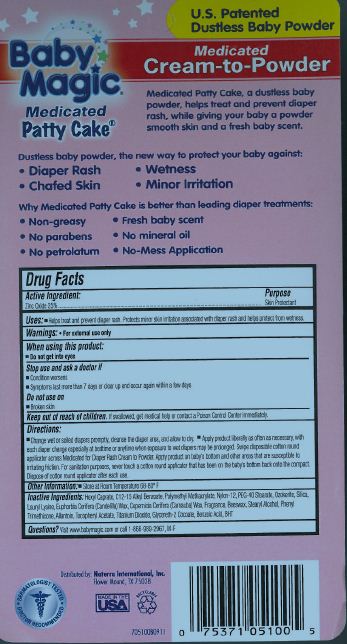 DRUG LABEL: Baby Magic Medicated Patty Cake
NDC: 45765-5100 | Form: CREAM
Manufacturer: Naterra  International INC.
Category: otc | Type: HUMAN OTC DRUG LABEL
Date: 20120101

ACTIVE INGREDIENTS: Zinc Oxide 2.75 g/11 g
INACTIVE INGREDIENTS: Allantoin; Benzoic Acid; YELLOW WAX; BUTYLATED HYDROXYTOLUENE; ALKYL (C12-15) BENZOATE; CARNAUBA WAX; CANDELILLA WAX; GLYCERETH-2 COCOATE; HEXYL DECANOATE; LAUROYL LYSINE; NYLON-12

Baby Magic Medicated Patty Cake

Active Ingredient : Zinc Oxide (28%)

PURPOSE

Uses: Helps treat and prevent diaper rash. Protects minor skin irritation associated with diaper rash and helps protect from wetness.

Keep out of reach of children. If swallowed ,get medical help or contact a Poison Control Center immediately.

Warnings; For external use only

INDICATIONS AND USAGE

Direction

Change wet and soiled diapers promptly; cleanse diaper area and allow to dry

Apply product liberally as often as necessary, with each diaper change specially at bedtime or anytime when exposure to wet diapers may be prolonged. Swipe disposable cotton round applicator across Medicated Patty Cake.

Apply baby powder on baby's bottom and other areas that can use powder and are susceptible to irritating friction. For sanitation purpose, never touch a cotton round applicator that has been on the baby's bottom back onto the powder.

Dispose of cotton round applicator after each use.

INACTIVE INGREDIENT

Allantoin ,Beeswax, Benzoic Acid, BHT, C12-15 Alkyl Benzoate, Copermicia Cerifera (Carnauba Wax) , Euphorbia Cerifera (Candellila) Wax, Fragrance , Glycereth-2 Cocoate , Hexyl Carprate , Lauryl Lysine , Nylon-12 , Ozokerite Wax, PEG-40 Stearate, Phenyl Trimethicone, Polymethylmethacrylate, Silica, Stearyl Alcohol, Titanium Dioxide, Tocopheryl Acetate

DOSAGE AND ADMINISTRATION

Enter section text here